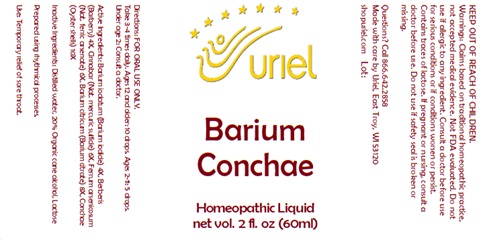 DRUG LABEL: Barium Conchae
NDC: 48951-2154 | Form: LIQUID
Manufacturer: Uriel Pharmacy Inc.
Category: homeopathic | Type: HUMAN OTC DRUG LABEL
Date: 20241025

ACTIVE INGREDIENTS: MERCURIC SULFIDE 6 [hp_X]/1 mL; BARIUM CITRATE 8 [hp_X]/1 mL; BERBERIS VULGARIS ROOT BARK 4 [hp_X]/1 mL; FERROUS ARSENATE 6 [hp_X]/1 mL; OSTREA EDULIS SHELL 10 [hp_X]/1 mL; BARIUM IODATE 4 [hp_X]/1 mL
INACTIVE INGREDIENTS: LACTOSE; ALCOHOL; WATER

Barium Conchae

INDICATIONS AND USAGE

Directions: FOR ORAL USE ONLY.

DOSAGE AND ADMINISTRATION

Take 3-4 times daily. Ages 12 and older: 10 drops. Ages 2-11: 5 drops. Under age 2: Consult a doctor.

ACTIVE INGREDIENT

Active Ingredients: Barium iodatum (Barium iodide) 4X, Berberis (Barberry) 4X, Cinnabar (Nat. mercuric sulfide) 6X, Ferrum arsenicosum (Nat. ferric arsenate) 6X, Barium citricum (Barium citrate) 8X, Conchae (Oyster shells) 10X

INACTIVE INGREDIENT

Inactive Ingredients: Distilled water, 20% Organic cane alcohol, Lactose

Prepared using rhythmical processes

PURPOSE

Use: Temporary relief of sore throat.

KEEP OUT OF REACH OF CHILDREN.

WARNINGS

Warnings: Do not use if allergic to any ingredient. Contains traces of lactose. Consult a doctor before use for serious conditions or if conditions worsen or persist. If pregnant or nursing, consult a doctor before use. Do not use if safety seal is broken or missing.

QUESTIONS

Questions? Call 866.642.2858 Made with care by Uriel, East Troy, WI 53120 shopuriel.com Lot: